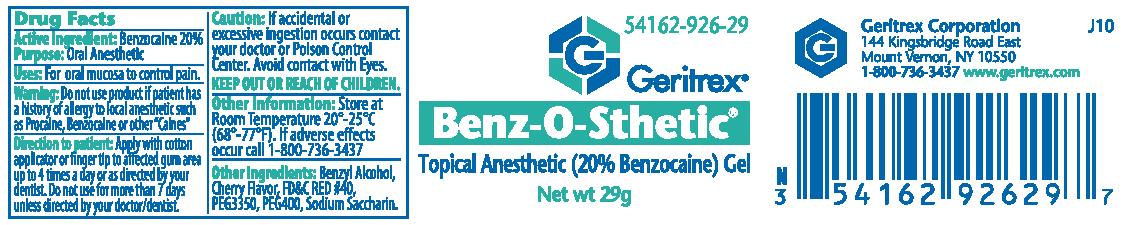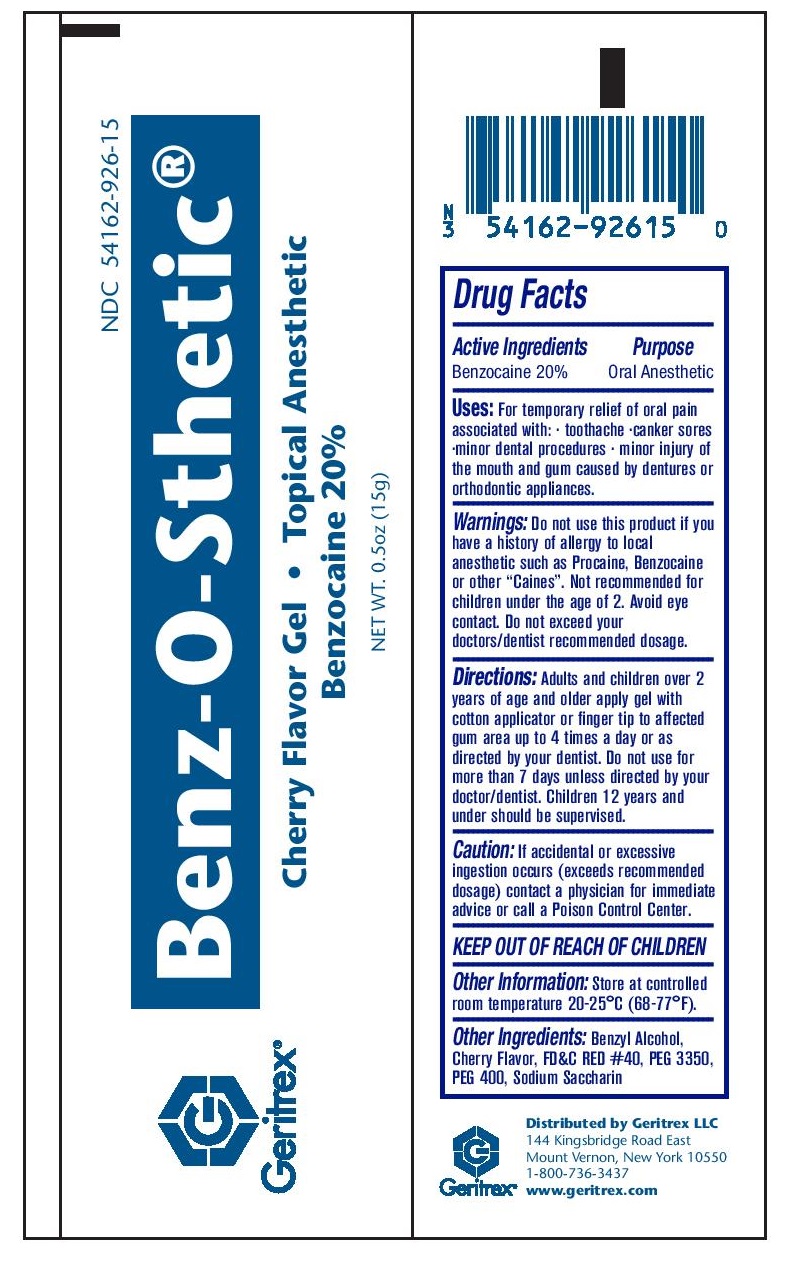 DRUG LABEL: Benz O Sthetic
NDC: 54162-926 | Form: GEL
Manufacturer: Geritrex LLC
Category: otc | Type: HUMAN OTC DRUG LABEL
Date: 20160810

ACTIVE INGREDIENTS: BENZOCAINE 20 g/100 g
INACTIVE INGREDIENTS: BENZYL ALCOHOL; FD&C RED NO. 40; POLYETHYLENE GLYCOL 400; POLYETHYLENE GLYCOL 3350; SACCHARIN SODIUM

Benz-O-Sthetic Gel

Drugs Facts

Active Ingredients Purpose
Benzocaine 20% Anesthetic

Uses

For temporary relief of oral pain associated with: · toothache ·canker sores ·minor dental
procedures · minor injury of the mouth and gum caused by dentures or orthodontic appliances.

Directions

Apply with cotton applicator or finger tip to affected gum area
up to 4 times a day or as directed by your dentist.

Do not use for more thatn 7 days.

Warnings

Do not use this product if you have a history of allergy to
local anesthetic such as Procaine, Benzocaine or other
“Caines”. Not recommended for children under the age of 2.

Other Ingredients

Benzyl Alcohol, Cherry Flavor, FD&C Red #40, PEG 3350, PEG 400, Sodium Saccharin

Storage

Store at controlled room temperature 20-25°C (68-77°F).

Keep out of reach of children